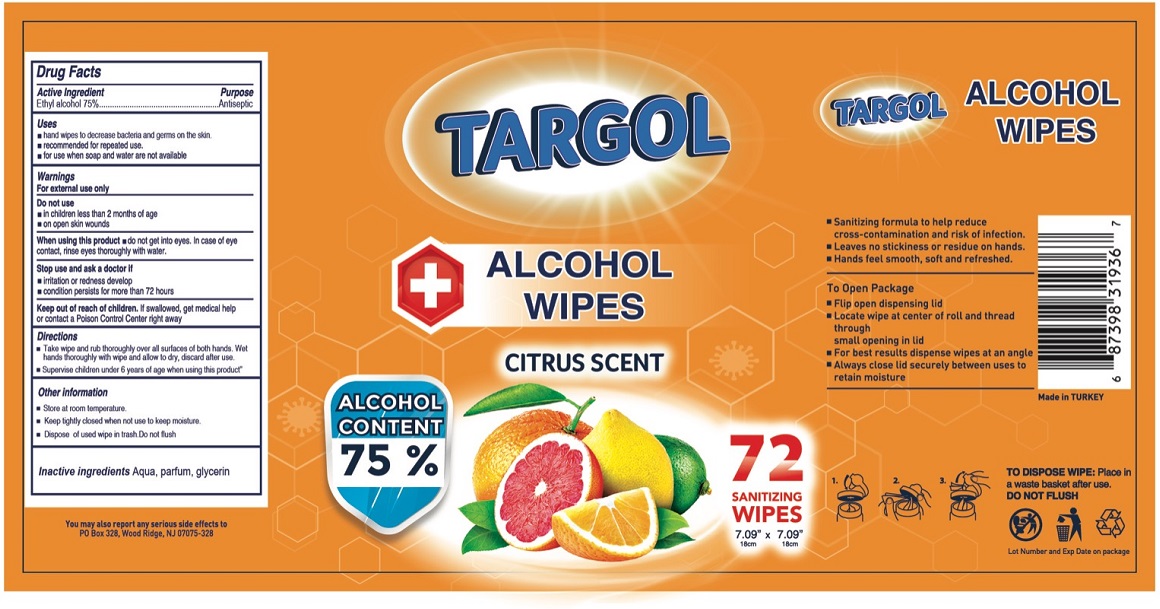 DRUG LABEL: TARGOL ALCOHOL WIPES - CITRUS SCENT
NDC: 80793-002 | Form: CLOTH
Manufacturer: HEDEF KIMYA SANAYI VE TICARET ANONIM SIRKETI
Category: otc | Type: HUMAN OTC DRUG LABEL
Date: 20201015

ACTIVE INGREDIENTS: ALCOHOL 75 g/100 g
INACTIVE INGREDIENTS: WATER; GLYCERIN

TARGOL ALCOHOL WIPES- CITRUS SCENT

Active Ingredient

Ethyl alcohol 75%

Purpose

Antiseptic

Uses

• hand wipes to decrease bacteria and germs on the skin.

• recommended for repeated use.

• for use when soap and water are not available

Warnings

For external use only

Do not use

• in children less than 2 months of age

• on open skin wounds

When using this product • do not get into eyes. In case of eye contact, rinse eyes thoroughly with water.

Stop use and ask a doctor if

• irritation or redness develop

• condition persists for more than 72 hours

Keep out of reach of children. If swallowed, get medical help or contact a Poison Control Center right away.

Directions

• Take wipe and rub thoroughly over all surfaces of both hands. Wet hands thoroughly with wipe and allow to dry, discard after use.

• Supervise children under 6 years of age when using this product"

Other information

• Store at room temperature.

• Keep tightly closed when not use to keep moisture.

• Dispose of used wipe in trash. Do not flush

Inactive ingredients

Aqua, parfum, glycerin

ALCOHOL CONTENT 75%

• Sanitizing formula to help reduce cross-contamination and risk of infection.

• Leaves no stickiness or residue on hands.

• Hands feel smooth, soft and refreshed.

To Open Package

• Flip open dispensing lid

• Locate wipe at center of roll and thread through small opening in lid

• For best results dispense wipes at an angle

• Always close lid securely between uses to retain moisture

Made in Turkey

TO DISPOSE WIPE: Place in a waste basket after use.

DO NOT FLUSH

You may also report any serious side effects to

PO BOX 328, Wood Ridge, NJ 07075-328